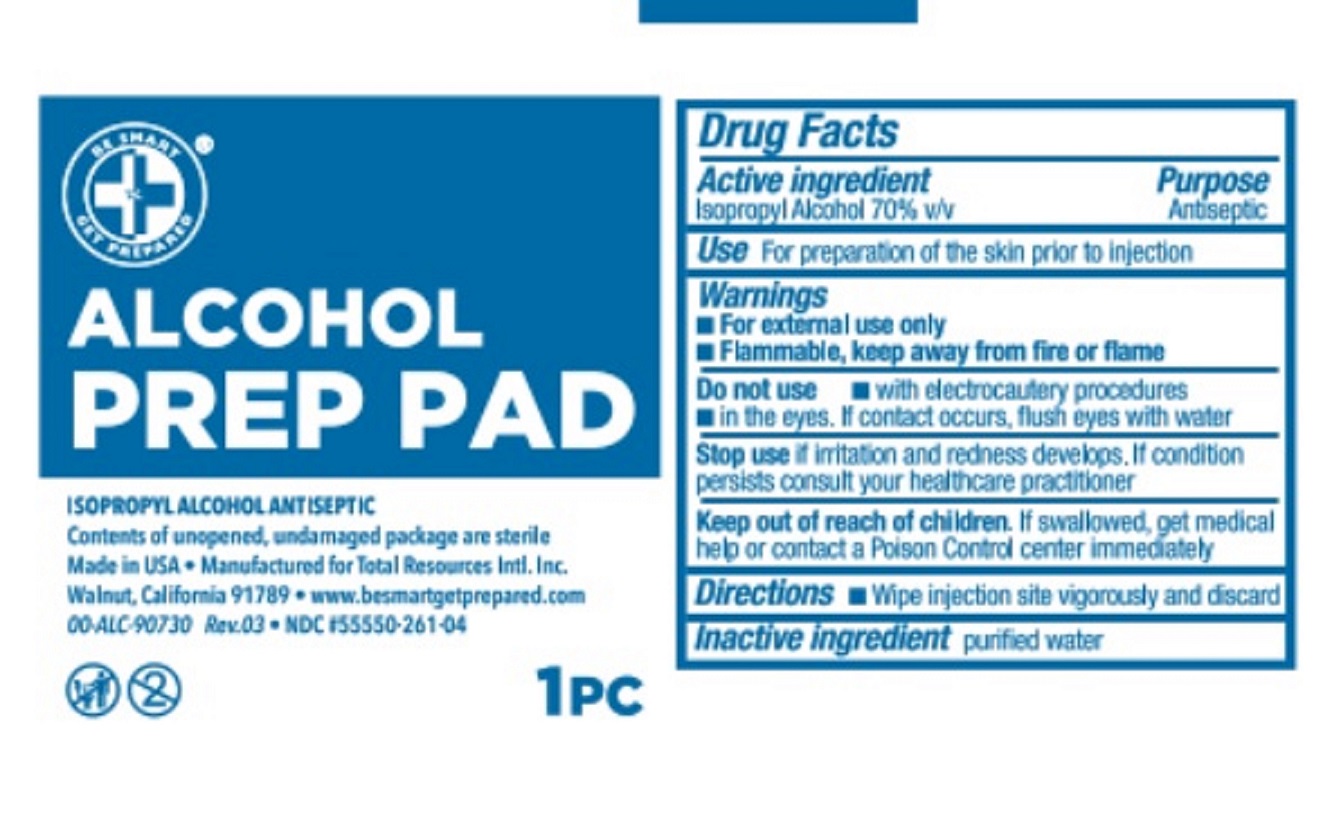 DRUG LABEL: Isopropyl Alcohol Antiseptic Pad
NDC: 55550-261 | Form: SWAB
Manufacturer: Total Resources International Inc.
Category: otc | Type: HUMAN OTC DRUG LABEL
Date: 20220831

ACTIVE INGREDIENTS: ISOPROPYL ALCOHOL 0.7 mL/1 mL
INACTIVE INGREDIENTS: WATER

Alcohol Prep Pads

Active Ingredients

Isopropyl Alcohol 70% v/v

Purpose

Antiseptic

Use

For the preparation of the skin prior to injection

Warnings

- For external use only
- Flammable, keep away from fire or flame

Do Not Use

• with electrocautery procedures

- in the eyes, If contact occurs, flush eyes with water

Keep out of reach of children

If swallowed, get medical help or contact a Poison Control Center Immediately.

Directions

Wipe Injection site vigorously and discard

Inactive Ingredient

purified water

DOSAGE AND ADMINISTRATION

Alcohol Prep Pad

1 Pc

One time use only